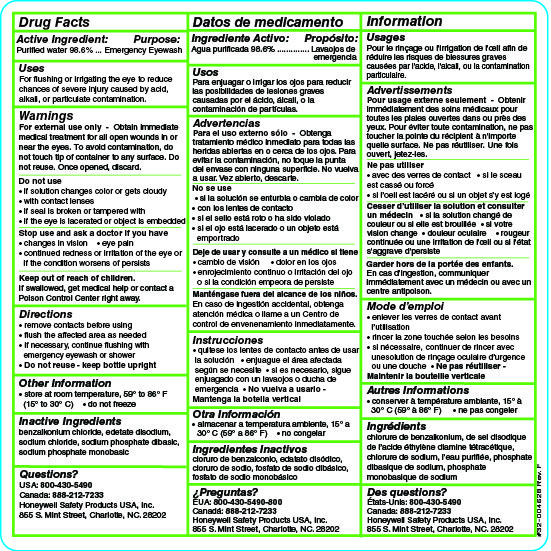 DRUG LABEL: Eyesaline Emergency Eyewash
NDC: 0498-0620 | Form: LIQUID
Manufacturer: Honeywell Safety Products USA, Inc.
Category: otc | Type: HUMAN OTC DRUG LABEL
Date: 20240614

ACTIVE INGREDIENTS: WATER 98.6 L/100 L
INACTIVE INGREDIENTS: EDETATE DISODIUM; BENZALKONIUM CHLORIDE; SODIUM CHLORIDE; SODIUM PHOSPHATE, MONOBASIC, MONOHYDRATE; SODIUM PHOSPHATE, DIBASIC

0498-0620: Emergency Eyewash Eyesaline

Active ingredient

Purified Water 98.6%

Purpose

Emergency Eyewash

Uses

For flushing or irrigating the eye to reduce chances of severe injury caused by acid, alkali, or particulate contamination

Warnings

For external use only

Obtain immediate medical treatment for all open wounds in or near the eyes

Do not use

- if solution changes color or gets cloudy
- with contact lenses
- in open wounds in or near the eyes
- if the eye is lacerated or object imbeded

Stop use and ask a doctor if you have

- changes in vision
- eye pain
- continued redness or irritation of the eyes or if the condition worsens or persists

Keep out of reach of children

If swallowed, get medical help or contact a Poison Control Center right away

Directions

remove contacts before using

flush the affected area as needed

if necessary continue flushing with emergency eyewash or shower

Other information

- store at rom temperature, 59o to 86o F (15o to 30o C)
- do not freeze
- to avoid contamination, do not touch tip of container to any surface
- once opened, discard
- do not reuse

Inactive ingredients

benzlkonium chloride, edetate disodium, sodium chloride, sodium phosphate dibasic, sodium phosphate monobasic

Questions?

1-800-430-5490

Honeywell Safety Products USA, Inc. 855 S. Mint Street, Charlotte, NC, 28202